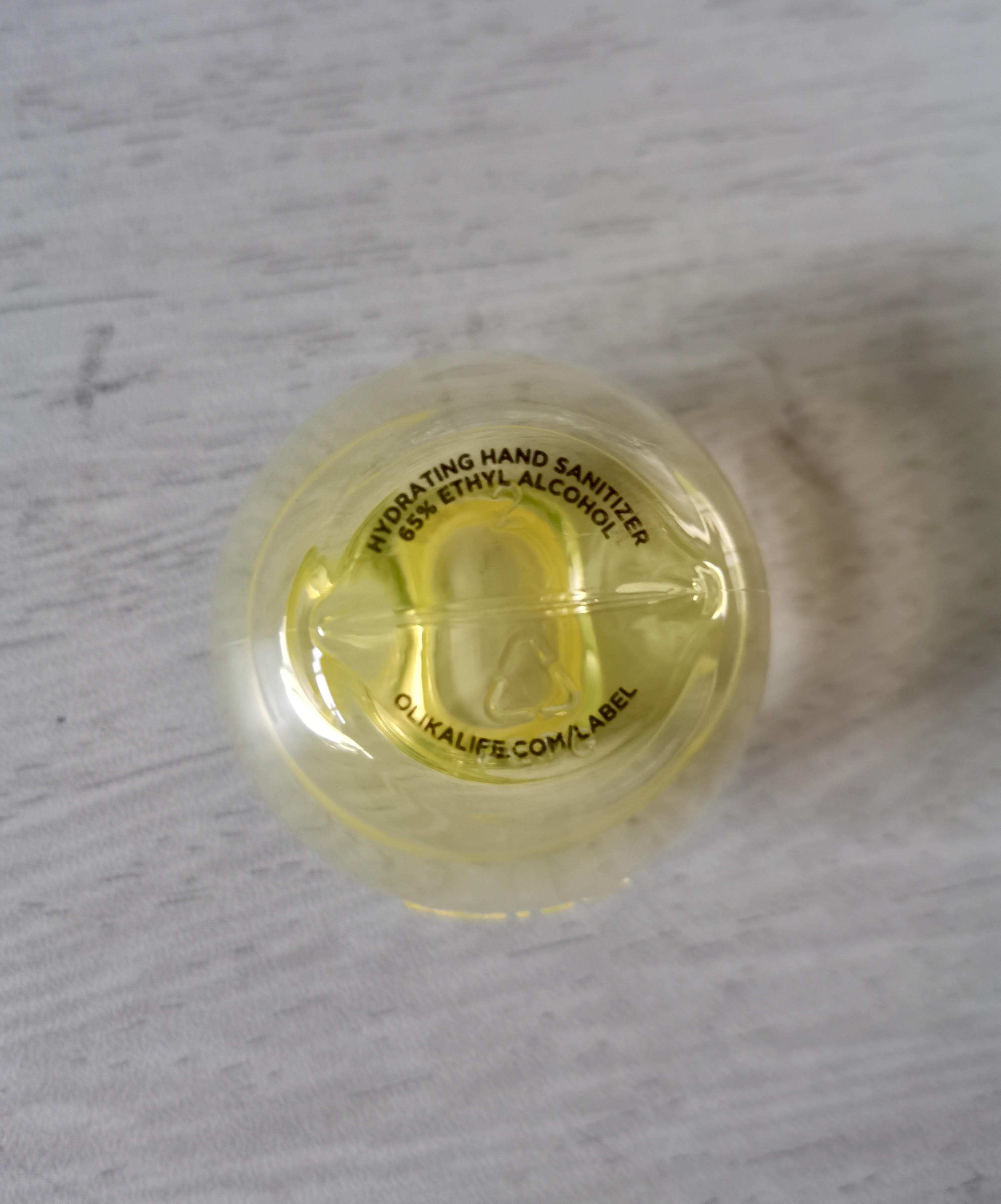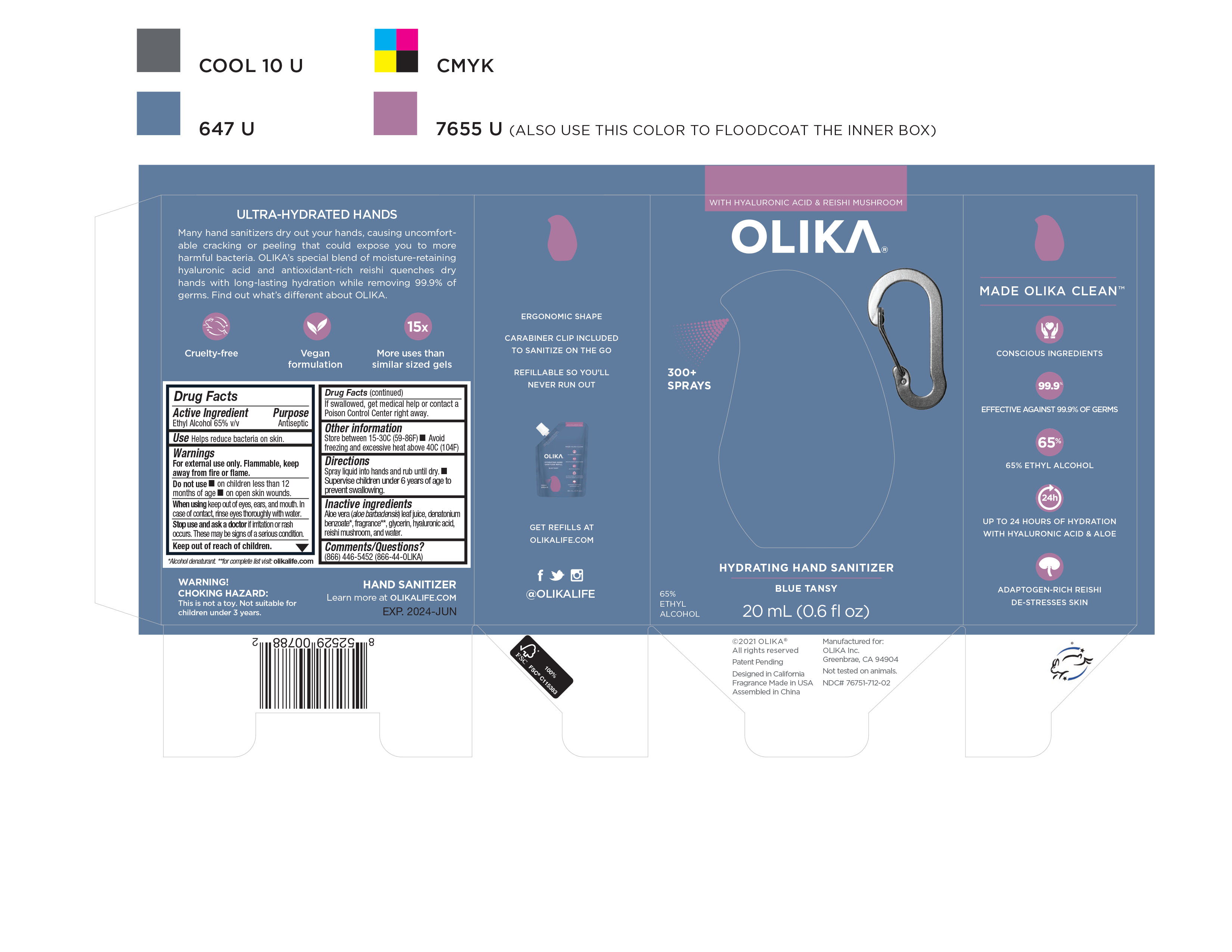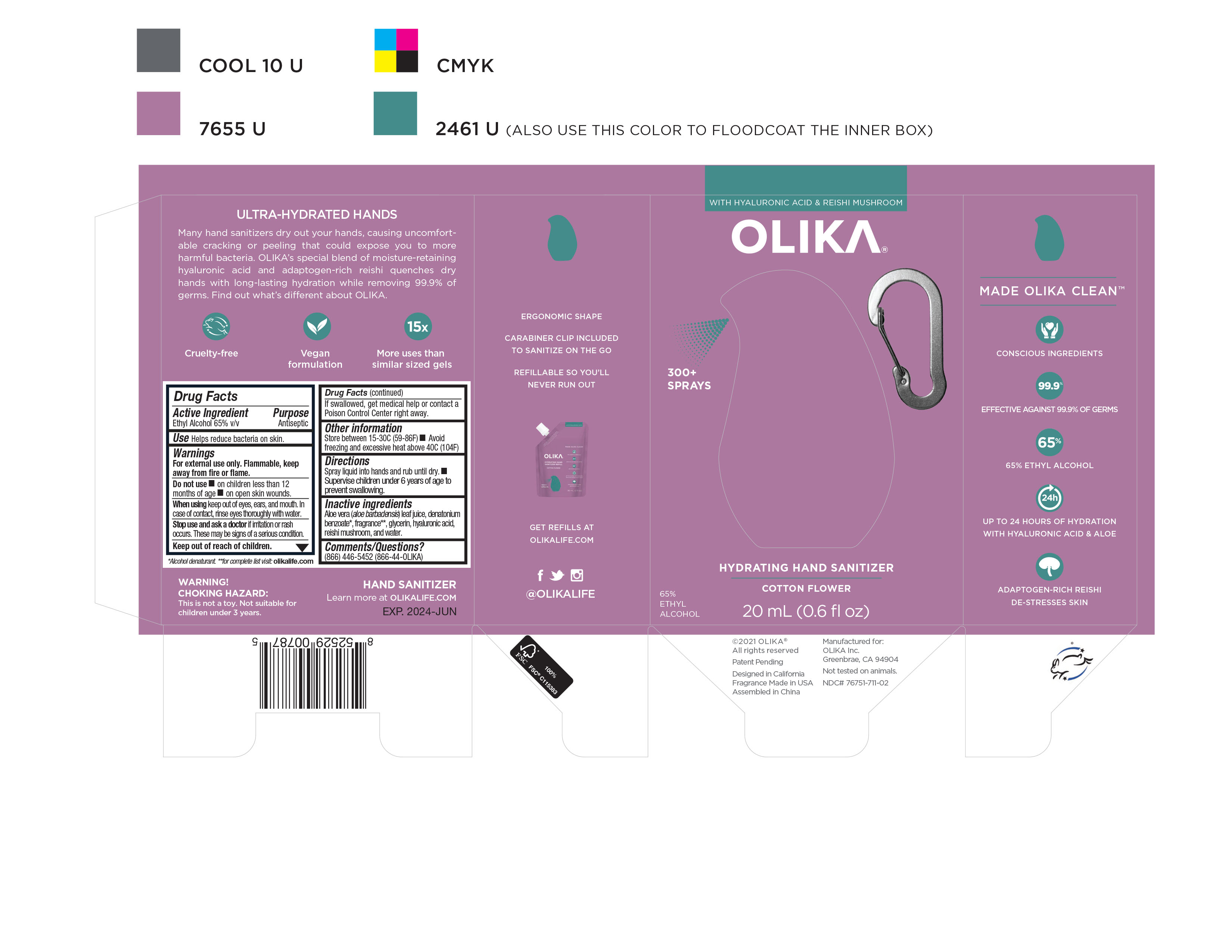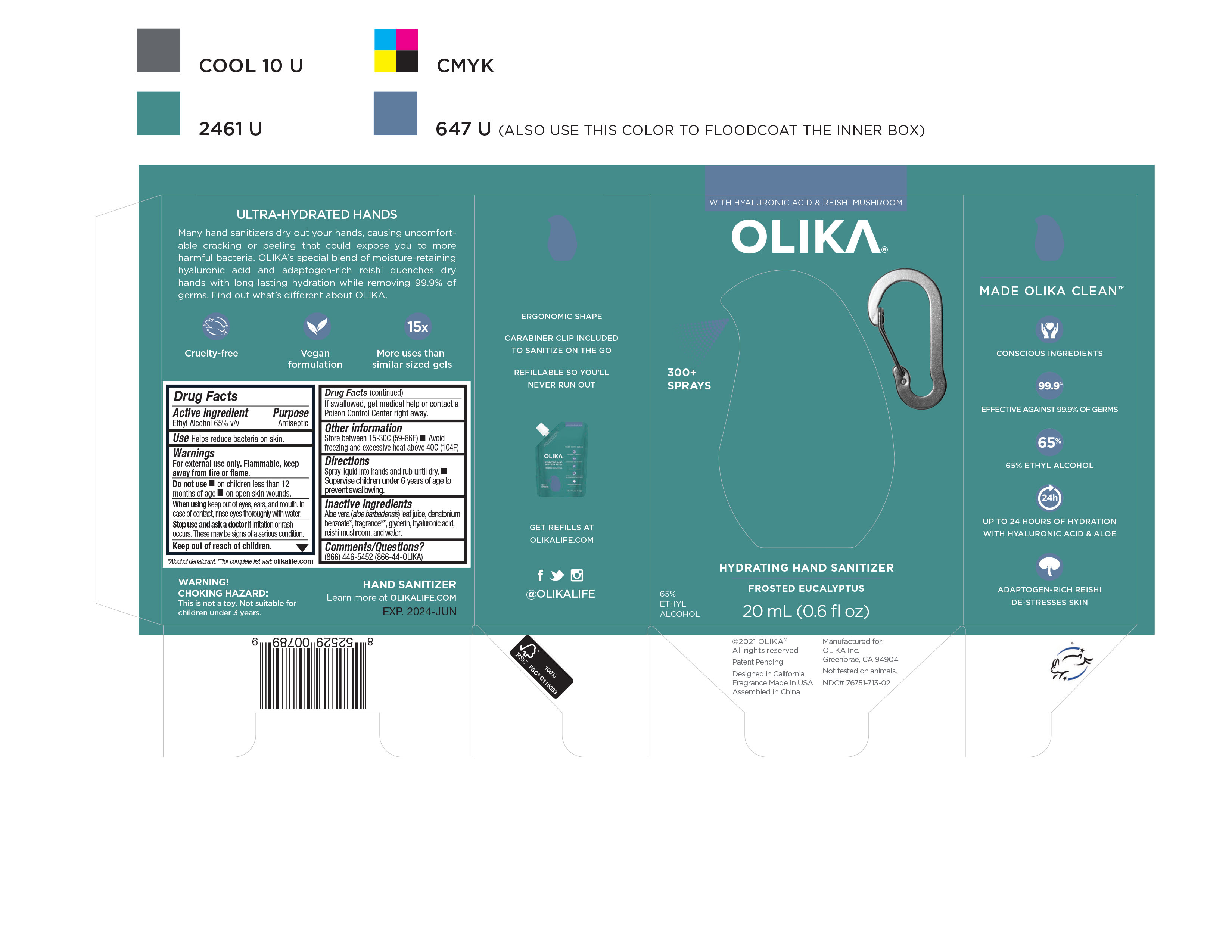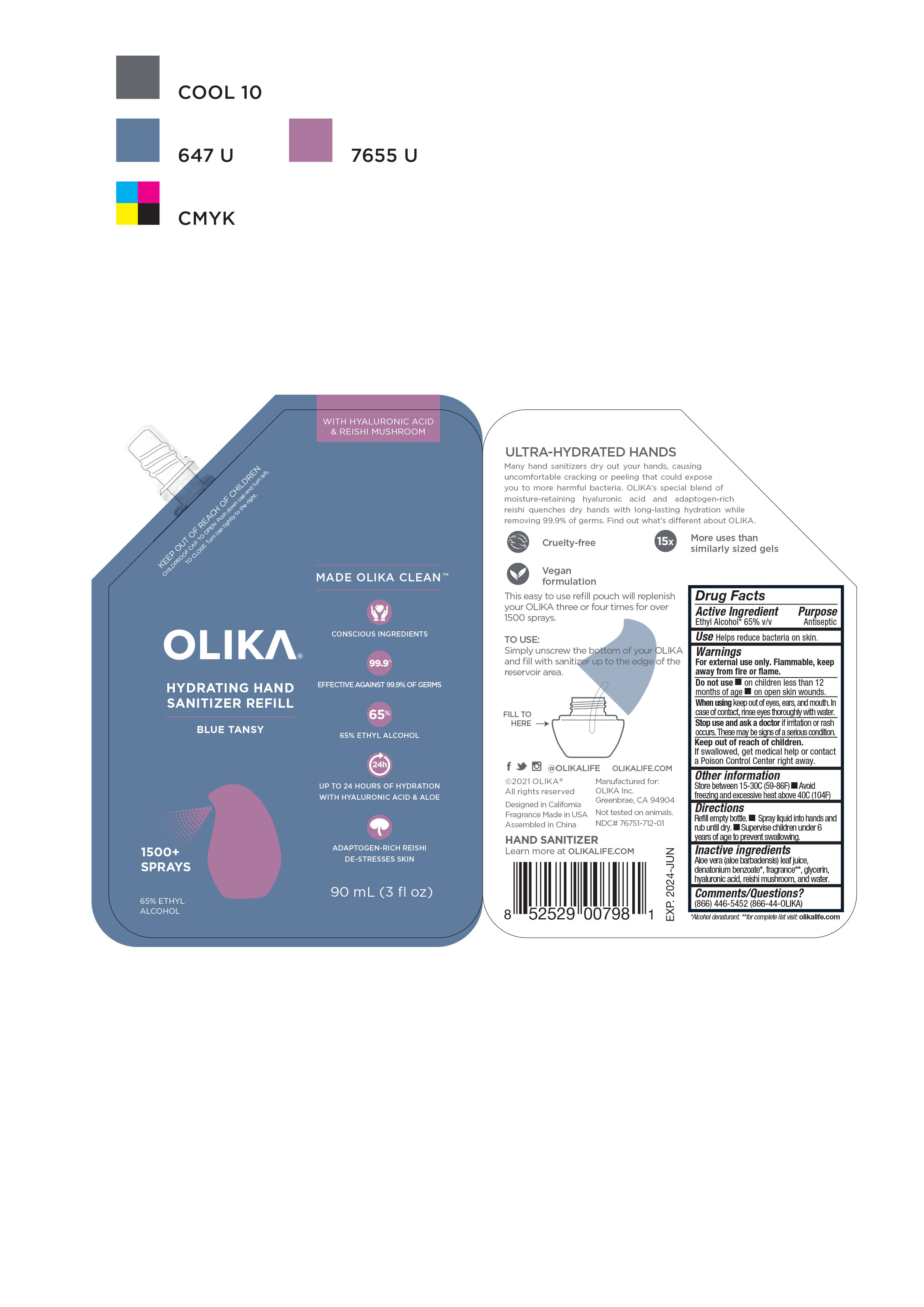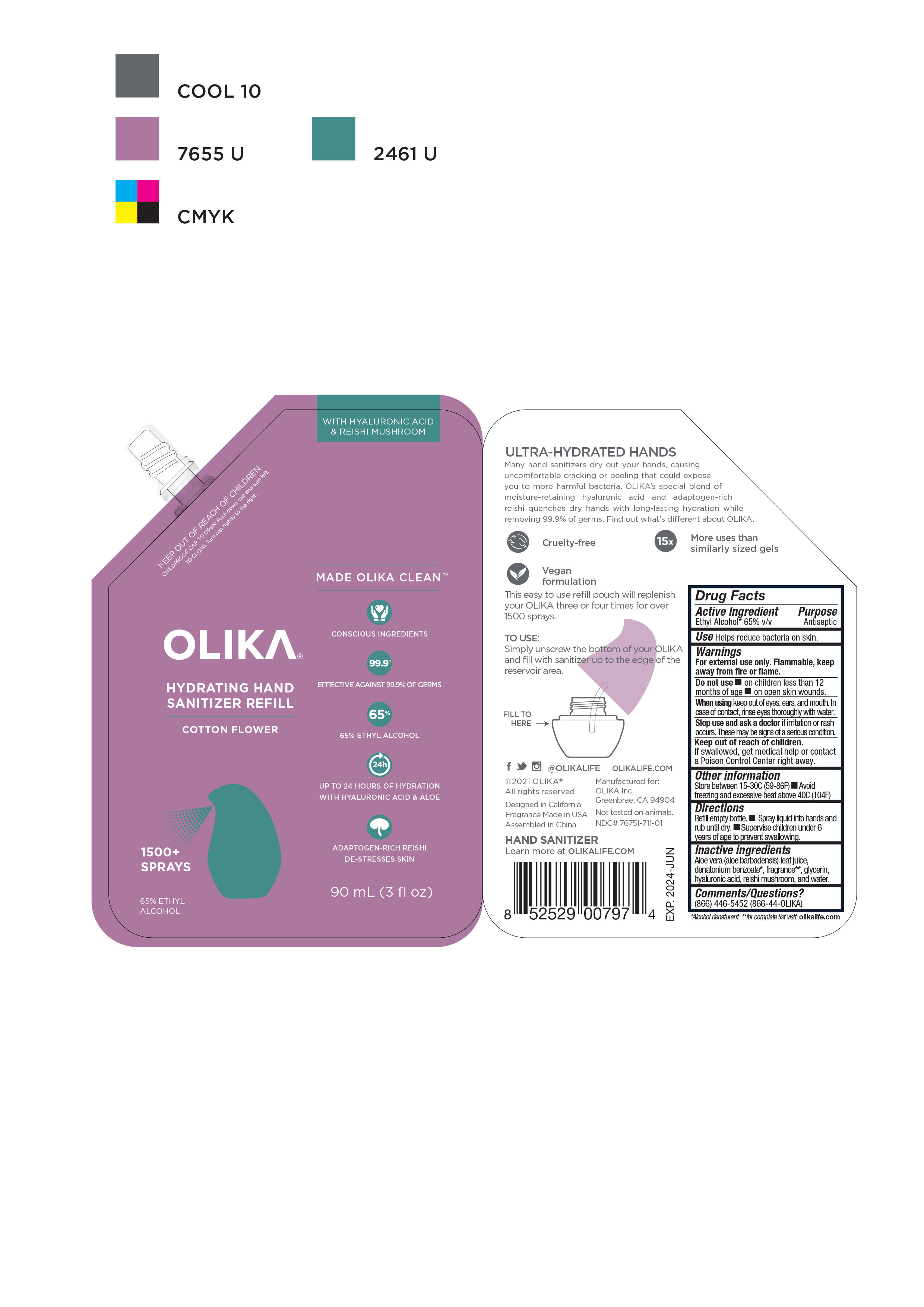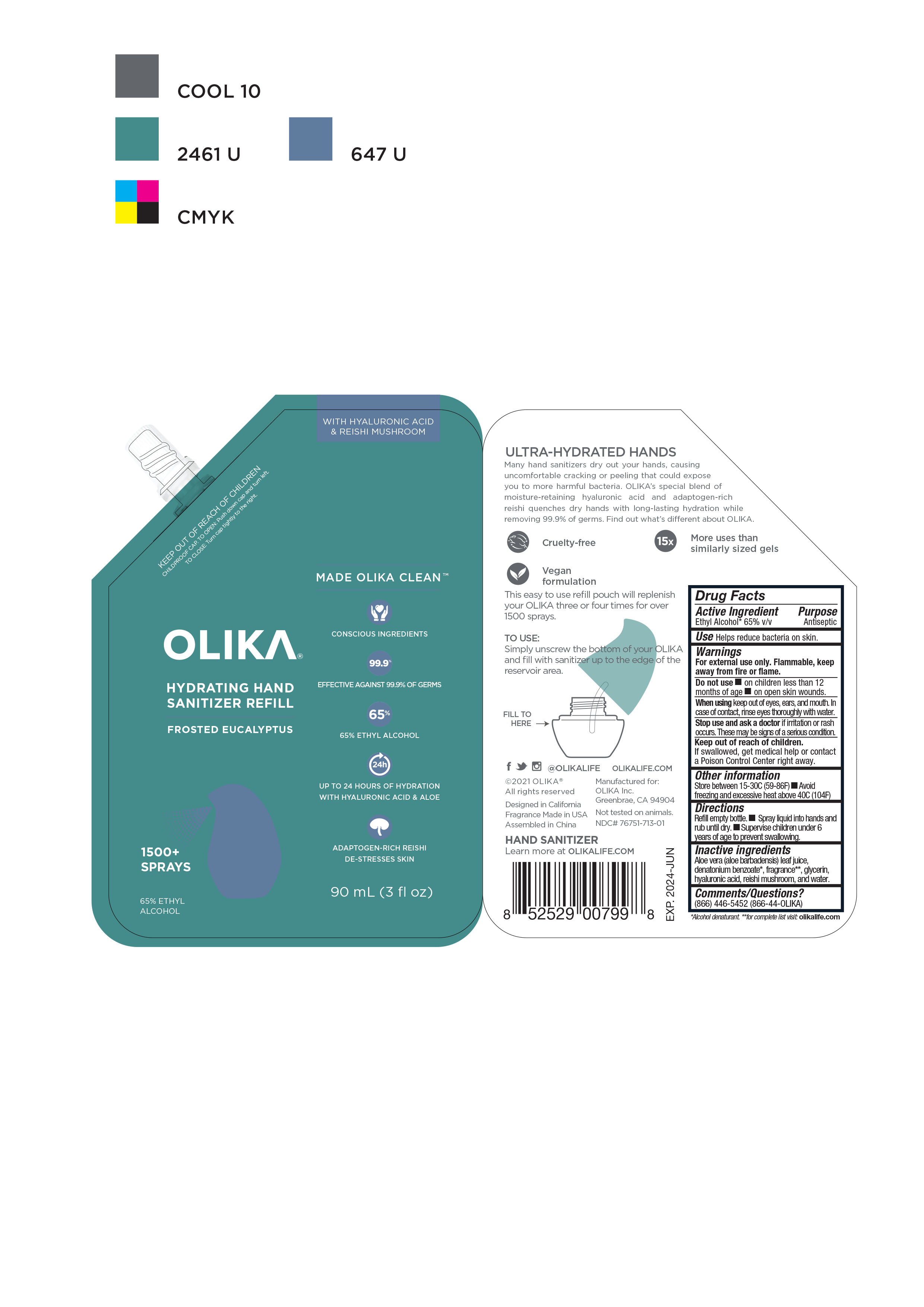 DRUG LABEL: Olika Hydrating Hand Sanitizer Frosted Eucalyptus
NDC: 76751-713 | Form: LIQUID
Manufacturer: Olika Inc.
Category: otc | Type: HUMAN OTC DRUG LABEL
Date: 20211210

ACTIVE INGREDIENTS: ALCOHOL 65 mL/100 mL
INACTIVE INGREDIENTS: ACETYL CEDRENE 0.01667 mL/100 mL; IONONE 0.00667 mL/100 mL; ETHYL LINALOOL 0.005 mL/100 mL; ETHYL BUTYRATE 0.005 mL/100 mL; FLORALOZONE 0.00417 mL/100 mL; METHYL BENZODIOXEPINONE 0.00167 mL/100 mL; GLYCERIN 4.2 mL/100 mL; WATER 29.78 mL/100 mL; NERYL ACETATE 0.00833 mL/100 mL; DIPROPYLENE GLYCOL 0.14825 mL/100 mL; 2-ISOBUTYL-4-METHYLTETRAHYDROPYRAN-4-OL 0.08333 mL/100 mL; ALLYL HEPTANOATE 0.00033 mL/100 mL; METHYL DIHYDROJASMONATE (SYNTHETIC) 0.075 mL/100 mL; DIHYDROMYRCENOL 0.03333 mL/100 mL; ETHYLENE BRASSYLATE 0.06667 mL/100 mL; 3-ISOCAMPHYLCYCLOHEXANOL, TRANS- 0.025 mL/100 mL; HEXYL ACETATE 0.00667 mL/100 mL; GERANYL ACETATE 0.005 mL/100 mL; ETHYL ACETOACETATE ETHYLENEGLYCOL KETAL 0.00167 mL/100 mL; PENTADECALACTONE 0.00167 mL/100 mL; CYCLOPENTANONE 0.00167 mL/100 mL; ETHYL 2,4-DECADIENOATE, (2E,4Z)- 0.00083 mL/100 mL; 4-(P-HYDROXYPHENYL)-2-BUTANONE 0.00083 mL/100 mL; HYALURONATE SODIUM 0.07 mL/100 mL; ALLYL .ALPHA.-IONONE 0.00083 mL/100 mL; ALLYL HEXANOATE 0.00083 mL/100 mL; ALLYL CYCLOHEXANEACETATE 0.00058 mL/100 mL; 3-HEXEN-1-OL, (3Z)- 0.0005 mL/100 mL; ALOE VERA LEAF 0.25 mL/100 mL; REISHI 0.2 mL/100 mL

Olika Mindfulness Hand Sanitizers- 3 scents in 20 mL, 90 mL

This is a hand sanitizer manufactured according to the1994 tentative final monograph for hand sanitizers and antiseptics. Final formulation finished product testing was performed to confirm efficacy and quality assurance.

The formulation comes in 2 package sizes: 20 mL and 90mL

Active Ingredient(s)

Ethyl Alcohol 65% v/v. Purpose: Antiseptic

Purpose

Antiseptic, Hand Sanitizer

Use

Helps reduce bacteria on skin.

Warnings

For external use only. Flammable. Keep away from heat or flame

Do not use

- in children less than 2 months of age
- on open skin wounds

When using this product keep out of eyes, ears, and mouth. In case of contact with eyes, rinse eyes thoroughly with water.
Stop use and ask a doctor if irritation or rash occurs. These may be signs of a serious condition.

Keep out of reach of children. If swallowed, get medical help or contact a Poison Control Center right away.

Directions

Spray liquid into hands and rub until dry. Use as often as needed.

Other information

- Store between 15-30C (59-86F)
- Avoid freezing and excessive heat above 40C (104F)

Inactive ingredients

aloe vera, fragrance, glycerin, hyaluronic acid, reishi mushrooms, water

20 mL Primary Container Spray Bottle Bottom Label

76751-711-02; 76751-712-02; 76751-713-02

20 mL Primary Container Spray Bottle Bottom Label

Package Label - Principal Display Panel and Information Panels

90 mL NDC: 76751-711-01

Package Label - Principal Display Panel and Information Panels

76751-711-02. 20 mL

Package Label - Principal Display Panel and Information Panels

76751-712-01 90 mL

Package Label - Principal Display Panel and Information Panels

76751-712-02. 20 mL

Package Label - Principal Display Panel and Information Panels

76751-713-01. 90mL

Package Label - Principal Display Panel and Information Panels

76751-713-02 20 mL